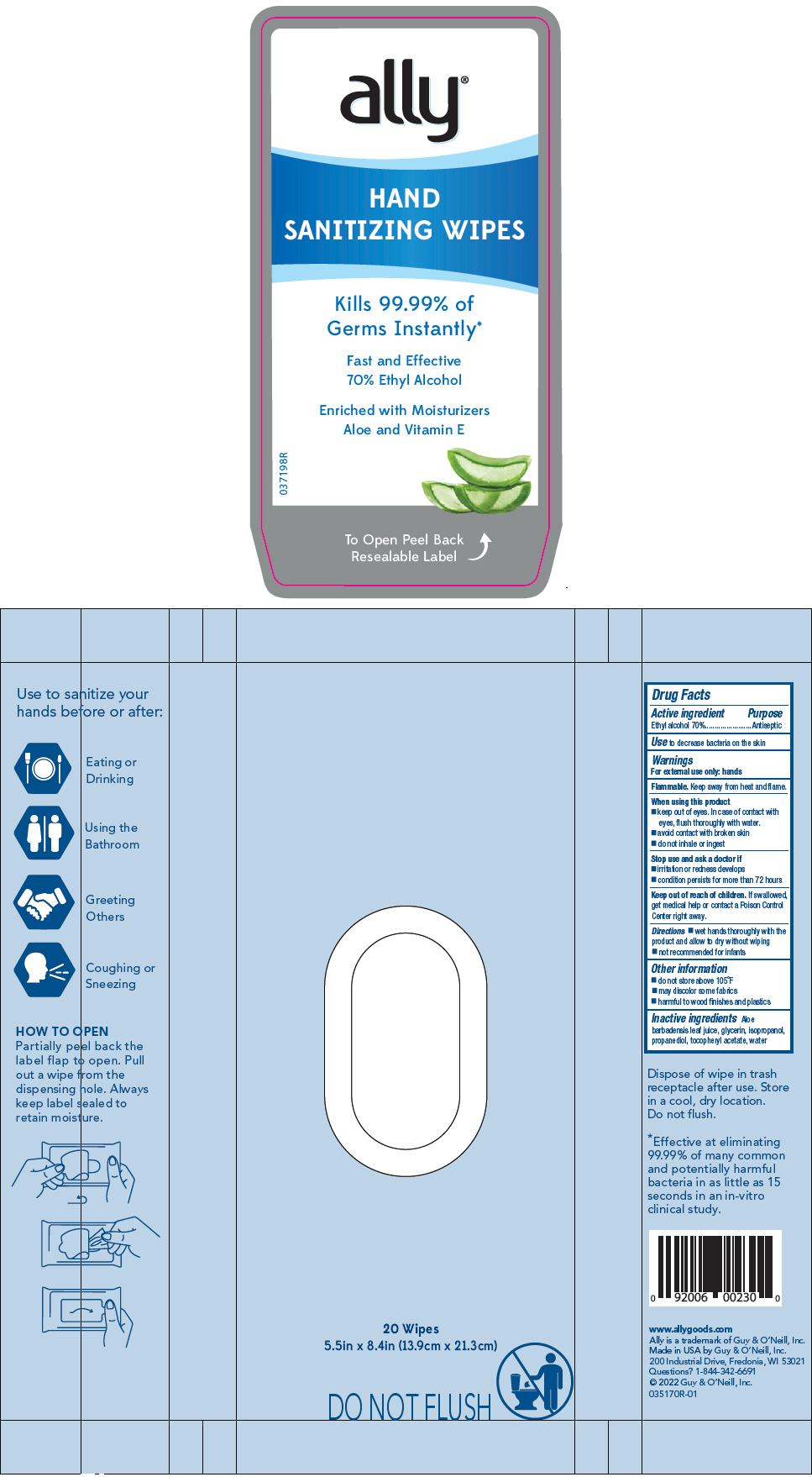 DRUG LABEL: Ally Hand Sanitizer Wipes
NDC: 50862-1310 | Form: CLOTH
Manufacturer: Guy & O'Neill, Inc.
Category: otc | Type: HUMAN OTC DRUG LABEL
Date: 20200417

ACTIVE INGREDIENTS: ALCOHOL 70 mL/100 1
INACTIVE INGREDIENTS: WATER 29 mL/100 1; ISOPROPYL ALCOHOL 1 mL/100 1; GLYCERIN 1 mL/100 1; PROPANEDIOL 0.5 mL/100 1; ALOE VERA LEAF 0.1 mL/100 1; .ALPHA.-TOCOPHEROL ACETATE 0.001 mL/100 1

Ally® Hand Sanitizer Wipes

Drug Facts

Active ingredient

Ethyl alcohol 70%

Purpose

Antiseptic

Use

to decrease bacteria on the skin

Warnings

For external use only: hands

Flammable. Keep away from heat and flame.

When using this product

- keep out of eyes. In case of contact with eyes, flush thoroughly with water.
- avoid contact with broken skin
- do not inhale or ingest

Stop use and ask a doctor if

- irritation or redness develops
- condition persists for more than 72 hours

Keep out of reach of children. If swallowed, get medical help or contact a Poison Control Center right away.

Directions

- wet hands thoroughly with the product and allow to dry without wiping
- not recommended for infants

Other Information

- do not store above 105°F
- may discolor some fabrics
- harmful to wood finishes and plastics

Inactive ingredients

Aloe barbadensis leaf juice, glycerin, isopropanol, propanediol, tocopheryl acetate, water

Questions?

1-844-342-6691

PRINCIPAL DISPLAY PANEL - 20 Wipe Pouch

ally®

HAND
SANITIZING WIPES

Kills 99.99% of
Germs Instantly*

Fast and Effective
70% Ethyl Alcohol

Enriched with Moisturizers
Aloe and Vitamin E

037198R

To Open Peel Back
Resealable Label

20 Wipes
5.5in x 8.4in (13.9cm x 21.3cm)

DO NOT FLUSH